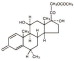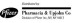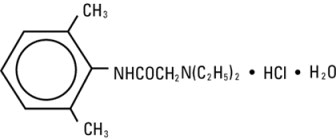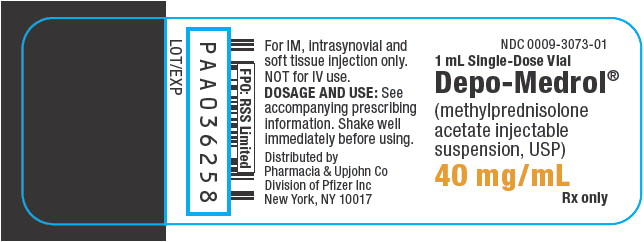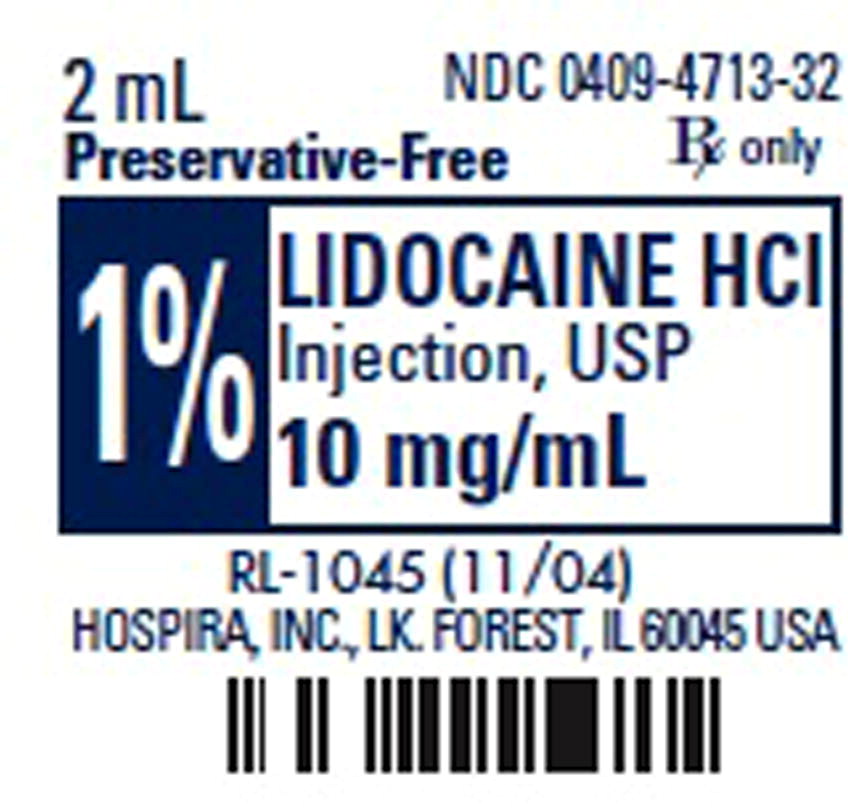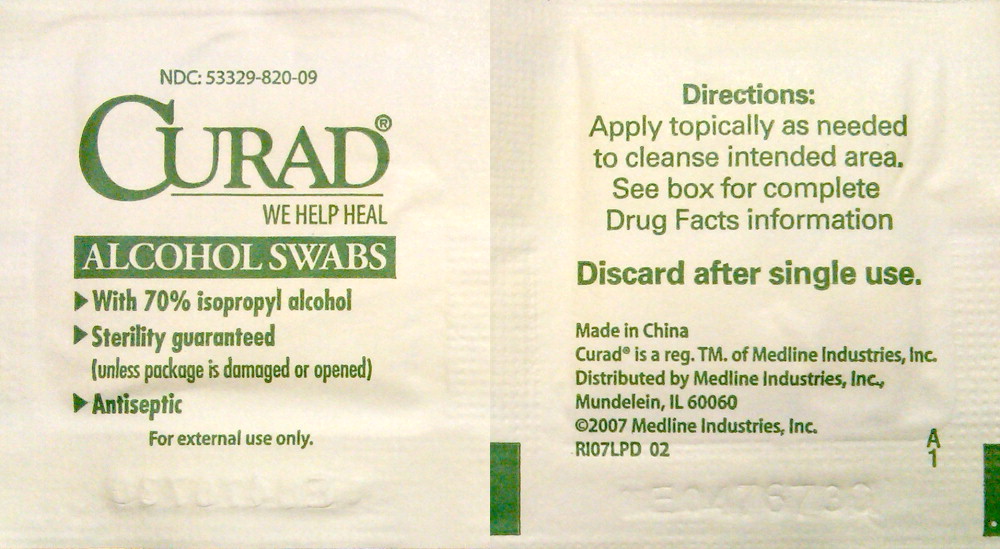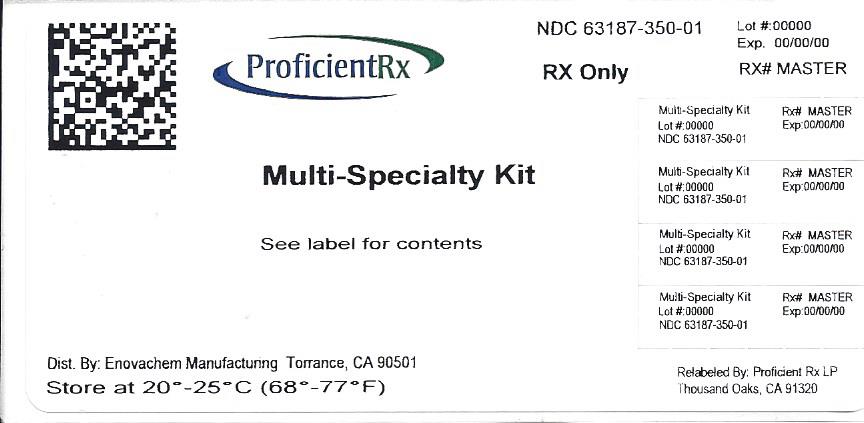 DRUG LABEL: Multi-Specialty Kit
NDC: 63187-350 | Form: KIT | Route: INTRAMUSCULAR
Manufacturer: Proficient Rx LP
Category: prescription | Type: HUMAN PRESCRIPTION DRUG LABEL
Date: 20140205

ACTIVE INGREDIENTS: Methylprednisolone Acetate 40 mg/1 mL; Lidocaine Hydrochloride 10 mg/1 mL; Isopropyl Alcohol 70 mL/100 mL
INACTIVE INGREDIENTS: Polyethylene Glycol 3350; Sodium Chloride; Sodium Hydroxide; Hydrochloric Acid; Sodium Chloride 7 mg/1 mL; Water; Sodium Hydroxide; Hydrochloric Acid; Water

DEPO-MEDROL®
(methylprednisolone acetate injectable suspension, USP)

Single-Dose Vial

Not For Intravenous Use

DESCRIPTION

DEPO-MEDROL is an anti-inflammatory glucocorticoid for intramuscular, intra-articular, soft tissue or intralesional injection. It is available as single-dose vials in two strengths: 40 mg/mL, 80 mg/mL.

Each mL of these preparations contains:

Methylprednisolone acetate | 40 mg | 80 mg
Polyethylene glycol 3350 | 29 mg | 28 mg
Myristyl-gamma-picolinium chloride | 0.195 mg | 0.189 mg

Sodium Chloride was added to adjust tonicity.

When necessary, pH was adjusted with sodium hydroxide and/or hydrochloric acid.

The pH of the finished product remains within the USP specified range (e.g., 3.0 to 7.0.)

The chemical name for methylprednisolone acetate is pregna-1,4-diene-3,20-dione, 21-(acetyloxy)-11,17-dihydroxy-6-methyl-,(6α,11β)- and the molecular weight is 416.51. The structural formula is represented below:

DEPO-MEDROL Sterile Aqueous Suspension contains methylprednisolone acetate which is the 6-methyl derivative of prednisolone. Methylprednisolone acetate is a white or practically white, odorless, crystalline powder which melts at about 215° with some decomposition. It is soluble in dioxane, sparingly soluble in acetone, alcohol, chloroform, and methanol, and slightly soluble in ether. It is practically insoluble in water.

CLINICAL PHARMACOLOGY

Glucocorticoids, naturally occurring and synthetic, are adrenocortical steroids.

Naturally occurring glucocorticoids (hydrocortisone and cortisone), which also have salt retaining properties, are used in replacement therapy in adrenocortical deficiency states. Their synthetic analogs are used primarily for their anti-inflammatory effects in disorders of many organ systems.

INDICATIONS AND USAGE

A. For Intramuscular Administration

When oral therapy is not feasible and the strength, dosage form, and route of administration of the drug reasonably lend the preparation to the treatment of the condition, the intramuscular use of DEPO-MEDROL Sterile Aqueous Suspension is indicated as follows:

Allergic States: Control of severe or incapacitating allergic conditions intractable to adequate trials of conventional treatment in asthma, atopic dermatitis, contact dermatitis, drug hypersensitivity reactions, seasonal or perennial allergic rhinitis, serum sickness, transfusion reactions.

Dermatologic Diseases: Bullous dermatitis herpetiformis, exfoliative dermatitis, mycosis fungoides, pemphigus, severe erythema multiforme (Stevens-Johnson syndrome).

Endocrine Disorders: Primary or secondary adrenocortical insufficiency (hydrocortisone or cortisone is the drug of choice; synthetic analogs may be used in conjunction with mineralocorticoids where applicable; in infancy, mineralocorticoid supplementation is of particular importance), congenital adrenal hyperplasia, hypercalcemia associated with cancer, nonsupportive thyroiditis.

Gastrointestinal Diseases: To tide the patient over a critical period of the disease in regional enteritis (systemic therapy) and ulcerative colitis.

Hematologic Disorders: Acquired (autoimmune) hemolytic anemia, congenital (erythroid) hypoplastic anemia (Diamond Blackfan anemia), pure red cell aplasia, select cases of secondary thrombocytopenia.

Miscellaneous: Trichinosis with neurologic or myocardial involvement, tuberculous meningitis with subarachnoid block or impending block when used concurrently with appropriate antituberculous chemotherapy.

Neoplastic Diseases: For palliative management of: leukemias and lymphomas.

Nervous System: Acute exacerbations of multiple sclerosis; cerebral edema associated with primary or metastatic brain tumor or craniotomy.

Ophthalmic Diseases: Sympathetic opthalmia, temporal arteritis, uveitis, ocular inflammatory conditions unresponsive to topical corticosteroids.

Renal Diseases: To induce diuresis or remission of proteinuria in idiopathic nephrotic syndrome, or that due to lupus erythematosus.

Respiratory Diseases: Berylliosis, fulminating or disseminated pulmonary tuberculosis when used concurrently with appropriate antituberculous chemotherapy, idiopathic eosinophilic pneumonias, symptomatic sarcoidosis.

Rheumatic Disorders: As adjunctive therapy for short-term administration (to tide the patient over an acute episode or exacerbation) in acute gouty arthritis; acute rheumatic carditis; ankylosing spondylitis; psoriatic arthritis; rheumatoid arthritis, including juvenile rheumatoid arthritis (selected cases may require low-dose maintenance therapy). For the treatment of dermatomyositis, polymyositis, and systemic lupus erythematosus.

B. For Intra-articular Or Soft Tissue Administration

(See WARNINGS)

DEPO-MEDROL is indicated as adjunctive therapy for short-term administration (to tide the patient over an acute episode or exacerbation) in acute gouty arthritis, acute and subacute bursitis, acute nonspecific tenosynovitis, epicondylitis, rheumatoid arthritis, synovitis of osteoarthritis.

C. For Intralesional Administration

DEPO-MEDROL is indicated for intralesional use in alopecia areata, discoid lupus erythematosus; keloids, localized hypertrophic, infiltrated inflammatory lesions of granuloma annulare, lichen planus, lichen simplex chronicus (neurodermatitis) and psoriatic plaques; necrobiosis lipoidica diabeticorum.

DEPO-MEDROL also may be useful in cystic tumors of an aponeurosis or tendon (ganglia).

CONTRAINDICATIONS

DEPO-MEDROL is contraindicated in patients with known hypersensitivity to the product and its constituents.

Intramuscular corticosteroid preparations are contraindicated for idiopathic thrombocytopenic purpura.

DEPO-MEDROL is contraindicated for intrathecal administration. This formulation of methylprednisolone acetate has been associated with reports of severe medical events when administered by this route.

DEPO-MEDROL is contraindicated in systemic fungal infections, except when administered as an intra-articular injection for localized joint conditions (see WARNINGS: Infections, Fungal Infections).

WARNINGS

General

This product is not suitable for multi-dose use. Following administration of the desired dose, any remaining suspension should be discarded.

Injection of DEPO-MEDROL may result in dermal and/or subdermal changes forming depressions in the skin at the injection site.

In order to minimize the incidence of dermal and subdermal atrophy, care must be exercised not to exceed recommended doses in injections. Multiple small injections into the area of the lesion should be made whenever possible. The technique of intra-articular and intramuscular injection should include precautions against injection or leakage into the dermis. Injection into the deltoid muscle should be avoided because of a high incidence of subcutaneous atrophy.

It is critical that, during administration of DEPO-MEDROL, appropriate technique be used and care taken to ensure proper placement of drug.

Rare instances of anaphylactoid reactions have occurred in patients receiving corticosteroid therapy (see ADVERSE REACTIONS).

Increased dosage of rapidly acting corticosteroids is indicated in patients on corticosteroid therapy subjected to any unusual stress before, during, and after the stressful situation.

Results from one multicenter, randomized, placebo-controlled study with methylprednisolone hemisuccinate, an IV corticosteroid, showed an increase in early (at 2 weeks) and late (at 6 months) mortality in patients with cranial trauma who were determined not to have other clear indications for corticosteroid treatment. High doses of systemic corticosteroids, including DEPO-MEDROL, should not be used for the treatment of traumatic brain injury.

Cardio-renal

Average and large doses of corticosteroids can cause elevation of blood pressure, salt and water retention, and increased excretion of potassium. These effects are less likely to occur with synthetic derivatives when used in large doses. Dietary salt restriction and potassium supplementation may be necessary. All corticosteroids increase calcium excretion.

Literature reports suggest an apparent association between use of corticosteroids and left ventricular free wall rupture after a recent myocardial infarction; therefore, therapy with corticosteroids should be used with great caution in these patients.

Endocrine

Hypothalamic-pituitary adrenal (HPA) axis suppression. Cushing's syndrome, and hyperglycemia: Monitor patients for these conditions with chronic use.

Corticosteroids can produce reversible HPA axis suppression with the potential for glucocorticosteroid insufficiency after withdrawal of treatment. Drug induced secondary adrenocortical insufficiency may be minimized by gradual reduction of dosage. This type of relative insufficiency may persist for months after discontinuation of therapy; therefore, in any situation of stress occurring during that period, hormone therapy should be reinstituted.

Infections

General

Persons who are on corticosteroids are more susceptible to infections than are healthy individuals. There may be decreased resistance and inability to localize infection when corticosteroids are used. Infections with any pathogen (viral, bacterial, fungal, protozoan, or helminthic) in any location of the body, may be associated with the use of corticosteroids alone or in combination with other immunosuppressive agents.

These infections may be mild, but can be severe and at times fatal. With increasing doses of corticosteroids, the rate of occurrence of infectious complications increases. Do not use intra-articularly, intrabursally, or for intratendinous administration for local effect in the presence of an acute infection. Corticosteroids may mask some signs of infection and new infections may appear during their use.

Fungal Infections

Corticosteroids may exacerbate systemic fungal infections and therefore should not be used in the presence of such infections unless they are needed to control drug interactions. There have been cases reported in which concomitant use of amphotericin B and hydrocortisone was followed by cardiac enlargement and congestive heart failure (see CONTRAINDICATIONS and PRECAUTIONS: Drug Interactions, Amphotericin B injection and potassium-depleting agents).

Special Pathogens

Latent disease may be activated or there may be an exacerbation of intercurrent infections due to pathogens, including those caused by Amoeba, Candida, Cryptococcus, Mycobacterium, Nocardia, Pneumocystis, and Toxoplasma.

It is recommended that latent amebiasis or active amebiasis be ruled out before initiating corticosteroid therapy in any patient who has spent time in the tropics or in any patient with unexplained diarrhea.

Similarly, corticosteroids should be used with great care in patients with known or suspected Strongyloides (threadworm) infestation. In such patients, corticosteroid-induced immunosuppression may lead to Strongyloides hyperinfection and dissemination with widespread larval migration, often accompanied by severe enterocolitis and potentially fatal gram-negative septicemia.

Corticosteroids should not be used in cerebral malaria. There is currently no evidence of benefit from steroids in this condition.

Tuberculosis

The use of corticosteroids in active tuberculosis should be restricted to those cases of fulminating or disseminated tuberculosis in which the corticosteroid is used for the management of the disease in conjunction with an appropriate antituberculous regimen.

If corticosteroids are indicated in patients with latent tuberculosis or tuberculin reactivity, close observation is necessary, as reactivation of the disease may occur. During prolonged corticosteroid therapy, these patients should receive chemoprophylaxis.

Vaccinations

Administration of live or live, attenuated vaccines is contraindicated in patients receiving immunosuppressive doses of corticosteroids. Killed or inactivated vaccines may be administered. However, the response to such vaccines cannot be predicted.

Immunization procedures may be undertaken in patients who are receiving corticosteroids as replacement therapy (e.g., for Addison's disease).

Viral Infections

Chicken pox and measles can have a more serious or even fatal course in pediatric and adult patients on corticosteroids. In pediatric and adult patients who have not had these diseases, particular care should be taken to avoid exposure. The contribution of the underlying disease and/or prior corticosteroid treatment to the risk is also not known. If exposed to chicken pox, prophylaxis with varicella zoster immune globulin (VZIG) may be indicated. If exposed to measles, prophylaxis with immunoglobulin (IG) may be indicated (see the respective package inserts for complete VZIG and IG prescribing information). If chicken pox develops, treatment with antiviral agents should be considered.

Ophthalmic

Use of corticosteroids may produce posterior subcapsular cataracts, glaucoma with possible damage to the optic nerves, and may enhance the establishment of secondary ocular infections due to bacteria, fungi, or viruses. The use of systemic corticosteroids is not recommended in the treatment of optic neuritis and may lead to an increase in the risk of new episodes. Corticosteroids should be used cautiously in patients with ocular herpes simplex because of corneal perforation. Corticosteroids should not be used in active ocular herpes simplex.

PRECAUTIONS

General

This product, like many other corticosteroids, is sensitive to heat. Therefore, it should not be autoclaved when it is desirable to sterilize the exterior of the vial.

The lowest possible dose of corticosteroid should be used to control the condition under treatment. When reduction in dosage is possible, the reduction should be gradual.

Since complications of treatment with glucocorticosteroids are dependent on the size of the dose and the duration of treatment, a risk/benefit decision must be made in each individual case as to dose and duration of treatment and as to whether daily or intermittent therapy should be used.

Karposi's sarcoma has been reported to occur in patients receiving corticosteroid therapy, most often for chronic conditions. Discontinuation of corticosteroids may result in clinical improvement.

Cardio-renal

As sodium retention with resultant edema and potassium loss may occur in patients receiving corticosteroids, these agents should be used with caution in patients with congestive heart failure or renal insufficiency.

Endocrine

Drug-induced secondary adrenocortical insufficiency may be minimized by gradual reduction of dosage. This type of relative insufficiency may persist for months after discontinuation of therapy; therefore, in any situation of stress occurring during that period, hormone therapy should be reinstituted. Since mineralocorticoid secretion may be impaired, salt and/or a mineralocorticoid should be administered concurrently.

Metabolic clearance of corticosteroids is decreased in hypothyroid patients and increased in hyperthyroid patients. Changes in thyroid status of the patient may necessitate adjustment in dosage.

Gastrointestinal

Steroids should be used with caution in active or latent peptic ulcers, diverticulitis, fresh intestinal anastomoses, and nonspecific ulcerative colitis, since they may increase the risk of perforation.

Signs of peritoneal irritation following gastrointestinal perforation in patients receiving corticosteroids may be minimal or absent.

Parenteral Administration

Intra-articularly injected corticosteroids may be systemically absorbed.

Appropriate examination of any joint fluid present is necessary to exclude a septic process.

A marked increase in pain accompanied by local swelling, further restriction of joint motion, fever, and malaise are suggestive of septic arthritis. If this complication occurs and diagnosis of sepsis is confirmed, appropriate antimicrobial therapy should be instituted.

Injection of a steroid into an infected site is to be avoided. Local injection of a steroid into a previously infected joint is not usually recommended.

Musculoskeletal

Corticosteroids decrease bone formation and increase bone resorption both through their effect on calcium regulation (e.g., decreasing absorption and increasing excretion) and inhibition of osteoblast function. This, together with a decrease in the protein matrix of the bone secondary to an increase in protein catabolism, and reduced sex hormone production, may lead to an inhibition of bone growth in pediatric patients and the development of osteoporosis at any age. Special consideration should be given to patients at increased risk of osteoporosis (i.e., postmenopausal women) before initiating corticosteroid therapy.

Neuro-psychiatric

Although controlled clinical trials have shown corticosteroids to be effective in speeding the resolution of acute exacerbations of multiple sclerosis, they do not show that corticosteroids affect the ultimate outcome or natural history of the disease. The studies do show that relatively high doses of corticosteroids are necessary to demonstrate a significant effect (see DOSAGE AND ADMINISTRATION).

An acute myopathy has been observed with the use of high doses of corticosteroids, most often occurring in patients with disorders of neuromuscular transmission (e.g., myasthenia gravis), or in patients receiving concomitant therapy with neuromuscular blocking drugs (e.g., pancuronium). This acute myopathy is generalized, may involve ocular and respiratory muscles, and may result in quadriparesis. Elevation of creatine kinase may occur. Clinical improvement or recovery after stopping corticosteroids may require weeks to years.

Psychic derangements may appear when corticosteroids are used, ranging from euphoria, insomnia, mood swings, personality changes, and severe depression to frank psychotic manifestations. Also, existing emotional instability or psychotic tendencies may be aggravated by corticosteroids.

Ophthalmic

Intraocular pressure may become elevated in some individuals. If steroid therapy is continued long-term, intraocular pressure should be monitored.

Corticosteroids should be used cautiously in patients with ocular herpes simplex for fear of corneal perforation.

Information for the Patient

Patients should be warned not to discontinue the use of corticosteroids abruptly or without medical supervision, to advise any medical attendants that they are taking corticosteroids and to seek medical advice at once should they develop a fever or other signs of infection.

Persons who are on corticosteroids should be warned to avoid exposure to chicken pox or measles. Patients should also be advised that if they are exposed, medical advice should be sought without delay.

Drug Interactions

Aminoglutethimide: Aminoglutethimide may lead to a loss of corticosteroid-induced adrenal suppression.

Amphotericin B injection and potassium-depleting agents: When corticosteroids are administered concomitantly with potassium depleting agents (e.g., amphotericin B, diuretics), patients should be observed closely for development of hypokalemia. There have been cases reported in which concomitant use of amphotericin B and hydrocortisone was followed by cardiac enlargement and congestive heart failure.

Antibiotics: Macrolide antibiotics have been reported to cause a significant decrease in corticosteroid clearance (see PRECAUTIONS: Drug Interactions, Hepatic Enzyme Inhibitors).

Anticholinesterases: Concomitant use of anticholinesterase agents and corticosteroids may produce severe weakness in patients with myasthenia gravis. If possible, anticholinesterase agents should be withdrawn at least 24 hours before initiating corticosteroid therapy.

Anticoagulants, oral: Coadministration of corticosteroids and warfarin usually results in inhibition of response to warfarin, although there have been some conflicting reports. Therefore, coagulation indices should be monitored frequently to maintain the desired anticoagulant effect.

Antidiabetics: Because corticosteroids may increase blood glucose concentration, dosage adjustments of antidiabetic agents may be required.

Antitubercular drugs: Serum concentrations of isoniazid may be decreased.

Cholestyramine: Cholestyramine may increase the clearance of oral corticosteroids.

Cyclosporine: Increased activity of both cyclosporine and corticosteroids may occur when the two are used concurrently. Convulsions have been reported with this concurrent use.

Digitalis glycosides: Patients on digitalis glycosides may be at risk of arrhythmias due to hypokalemia.

Estrogens, including oral contraceptives: Estrogens may decrease the hepatic metabolism of certain corticosteroids, thereby increasing their effect.

Hepatic Enzyme Inducers (e.g., barbiturates, phenytoin, carbamazepine, rifampin): Drugs which induce cytochrome P450 3A4 enzyme activity may enhance the metabolism of corticosteroids and require that the dosage of the corticosteroid be increased.

Hepatic Enzyme Inhibitors (e.g., ketoconazole, macrolide antibiotics such as erythromycin and troleandomycin): Drugs which inhibit cytochrome P450 3A4 have the potential to result in increased plasma concentrations of corticosteroids.

Ketoconazole: Ketoconazole has been reported to significantly decrease the metabolism of certain corticosteroids by up to 60%, leading to an increased risk of corticosteroid side effects.

Nonsteroidal anti-inflammatory drugs (NSAIDs): Concomitant use of aspirin (or other nonsteroidal anti-inflammatory agents) and corticosteroids increases the risk of gastrointestinal side effects. Aspirin should be used cautiously in conjunction with corticosteroids in hypoprothrombinemia. The clearance of salicylates may be increased with concurrent use of corticosteroids.

Skin tests: Corticosteroids may suppress reactions to skin tests.

Vaccines: Patients on prolonged corticosteroid therapy may exhibit a diminished response to toxoids and live or inactivated vaccines due to inhibition of antibody response. Corticosteroids may also potentiate the replication of some organisms contained in live attenuated vaccines. Routine administration of vaccines or toxoids should be deferred until corticosteroid therapy is discontinued if possible (see WARNINGS: Infections, Vaccinations).

Carcinogenesis, Mutagenesis, Impairment of Fertility

No adequate studies have been conducted in animals to determine whether corticosteroids have a potential for carcinogenesis or mutagenesis.

Steroids may increase or decrease motility and number of spermatozoa in some patients.

Pregnancy: Teratogenic Effects: Pregnancy Category C

TERATOGENIC EFFECTS

Corticosteroids have been shown to be teratogenic in many species when given in doses equivalent to the human dose. Animal studies in which corticosteroids have been given to pregnant mice, rats, and rabbits have yielded an increased incidence of cleft palate in the offspring. There are no adequate and well-controlled studies in pregnant women. Corticosteroids should be used during pregnancy only if the potential benefit justifies the potential risk to the fetus. Infants born to mothers who have received corticosteroids during pregnancy should be carefully observed for signs of hypoadrenalism.

Nursing Mothers

Systemically administered corticosteroids appear in human milk and could suppress growth, interfere with endogenous corticosteroid production, or cause other untoward effects. Because of the potential for serious adverse reactions in nursing infants from corticosteroids, a decision should be made whether to discontinue nursing or discontinue the drug, taking into account the importance of the drug to the mother.

Pediatric Use

The efficacy and safety of corticosteroids in the pediatric population are based on the well-established course of effect of corticosteroids which is similar in pediatric and adult populations. Published studies provide evidence of efficacy and safety in pediatric patients for the treatment of nephritic syndrome (patients >2 years of age) and aggressive lymphomas and leukemias (patients >1 month of age). Other indications for pediatric use of corticosteroids (e.g., severe asthma and wheezing) are based on adequate and well-controlled clinical trials conducted in adults, on the premises that the course of the diseases and their pathophysiology are considered to be substantially similar in both populations.

The adverse effects of corticosteroids in pediatric patients are similar to those in adults (see ADVERSE REACTIONS). Like adults, pediatric patients should be carefully observed with frequent measurements of blood pressure, weight, height, intraocular pressure, and clinical evaluation for the presence of infection, psychosocial disturbances, thromboembolism, peptic ulcers, cataracts, and osteoporosis. Pediatric patients who are treated with corticosteroids by any route, including systemically administered corticosteroids, may experience a decrease in their growth velocity. This negative impact of corticosteroids on growth has been observed at low systemic doses and in the absence of laboratory evidence of HPA axis suppression (i.e., cosyntropin stimulation and basal cortisol plasma levels). Growth velocity may therefore be a more sensitive indicator of systemic corticosteroid exposure in pediatric patients than some commonly used tests of HPA axis function. The linear growth of pediatric patients treated with corticosteroids should be monitored, and the potential growth effects of prolonged treatment should be weighed against clinical benefits obtained and the availability of treatment alternatives. In order to minimize the potential growth effects of corticosteroids, pediatric patients should be titrated to the lowest effective dose.

Geriatric Use

Clinical studies did not include sufficient numbers of subjects aged 65 and over to determine whether they respond differently from younger subjects. Other reported clinical experience has not identified differences in responses between the elderly and younger patients. In general, dose selection for an elderly patient should be cautious, usually starting at the low end of the dosing range, reflecting the greater frequency of decreased hepatic, renal, or cardiac function, and of concomitant disease or other drug therapy.

ADVERSE REACTIONS

The following adverse reactions have been reported with DEPO-MEDROL or other corticosteroids:

Allergic reactions: Allergic or hypersensitivity reactions, anaphylactoid reaction, anaphylaxis, angioedema.

Cardiovascular: Bradycardia, cardiac arrest, cardiac arrhythmias, cardiac enlargement, circulatory collapse, congestive heart failure, fat embolism, hypertension, hypertrophic cardiomyopathy in premature infants, myocardial rupture following recent myocardial infarction (see WARNINGS), pulmonary edema, syncope, tachycardia, thromboembolism, thrombophlebitis, vasculitis.

Dermatologic: Acne, allergic dermatitis, cutaneous and subcutaneous atrophy, dry scaly skin, ecchymoses and petechiae, edema, erythema, hyperpigmentation, hypopigmentation, impaired wound healing, increased sweating, rash, sterile abscess, striae, suppressed reactions to skin tests, thin fragile skin, thinning scalp hair, urticaria.

Endocrine: Decreased carbohydrate and glucose tolerance, development of cushingoid state, glycosuria, hirsutism, hypertrichosis, increased requirements for insulin or oral hypoglycemic agents in diabetes, manifestations of latent diabetes mellitus, menstrual irregularities, secondary adrenocortical and pituitary unresponsiveness (particularly in times of stress, as in trauma, surgery, or illness), suppression of growth in pediatric patients.

Fluid and electrolyte disturbances: Congestive heart failure in susceptible patients, fluid retention, hypokalemic alkalosis, potassium loss, sodium retention.

Gastrointestinal: Abdominal distention, bowel/bladder dysfunction (after intrathecal administration), elevation in serum liver enzyme levels (usually reversible upon discontinuation), hepatomegaly, increased appetite, nausea, pancreatitis, peptic ulcer with possible subsequent perforation and hemorrhage, perforation of the small and large intestine (particularly in patients with inflammatory bowel disease), ulcerative esophagitis.

Metabolic: Negative nitrogen balance due to protein catabolism.

Musculoskeletal: Aseptic necrosis of femoral and humeral heads, calcinosis (following intra-articular or intra-lesional use), Charcot-like arthropathy, loss of muscle mass, muscle weakness, osteoporosis, pathologic fracture of long bones, postinjection flare (following intra-articular use), steroid myopathy, tendon rupture, vertebral compression fractures.

Neurologic/Psychiatric: Convulsions, depression, emotional instability, euphoria, headache, increased intracranial pressure with papilledema (pseudotumor cerebri) usually following discontinuation of treatment, insomnia, mood swings, neuritis, neuropathy, paresthesia, personality changes, psychic disorders, vertigo.

Ophthalmic: Exophthalmoses, glaucoma, increased intraocular pressure, posterior subcapsular cataracts.

Other: Abnormal fat deposits, decreased resistance to infection, hiccups, increased or decreased motility and number of spermatozoa, injection site infections following non-sterile administration (see WARNINGS), malaise, moon face, weight gain.

The following adverse reactions have been reported with the following routes of administration:

Intrathecal/Epidural: Arachnoiditis, bowel/bladder dysfunction, headache, meningitis, parapareisis/paraplegia, seizures, sensory disturbances.

Intranasal: Allergic reactions, rhinitis, temporary/permanent visual impairment including blindness.

Ophthalmic: Increased intraocular pressure, infection, ocular and periocular inflammation including allergic reactions, residue or slough at injection site, temporary/permanent visual impairment including blindness.

Miscellaneous injection sites (scalp, tonsillar fauces, sphenopalatine ganglion): blindness.

OVERDOSAGE

Treatment of acute overdosage is by supportive and symptomatic therapy. For chronic overdosage in the face of severe disease requiring continuous steroid therapy, the dosage of the corticosteroid may be reduced only temporarily, or alternate day treatment may be introduced.

DOSAGE AND ADMINISTRATION

Because of possible physical incompatibilities, DEPO-MEDROL Sterile Aqueous Suspension should not be diluted or mixed with other solutions.

The initial dosage of parenterally administered DEPO-MEDROL will vary from 4 to 120 mg, depending on the specific disease entity being treated. However, in certain overwhelming, acute, life-threatening situations, administration in dosages exceeding the usual dosages may be justified and may be in multiples of the oral dosages.

It Should Be Emphasized that Dosage Requirements Are Variable and Must Be Individualized on the Basis of the Disease Under Treatment and the Response of the Patient. After a favorable response is noted, the proper maintenance dosage should be determined by decreasing the initial drug dosage in small decrements at appropriate time intervals until the lowest dosage which will maintain an adequate clinical response is reached. Situations which may make dosage adjustments necessary are changes in clinical status secondary to remissions or exacerbations in the disease process, the patient's individual drug responsiveness, and the effect of patient exposure to stressful situations not directly related to the disease entity under treatment. In this latter situation, it may be necessary to increase the dosage of the corticosteroid for a period of time consistent with the patient's condition. If after long-term therapy the drug is to be stopped, it is recommended that it be withdrawn gradually rather than abruptly.

A. Administration for Local Effect

Therapy with DEPO-MEDROL does not obviate the need for the conventional measures usually employed. Although this method of treatment will ameliorate symptoms, it is in no sense a cure and the hormone has no effect on the cause of the inflammation.

1. Rheumatoid Arthritis and Osteoarthritis. The dose for intra-articular administration depends upon the size of the joint and varies with the severity of the condition in the individual patient. In chronic cases, injections may be repeated at intervals ranging from one to five or more weeks, depending upon the degree of relief obtained from the initial injection. The doses in the following table are given as a general guide:

Size of Joint | Examples | Range of Dosage
Large | Knees Ankles Shoulders | 20 to 80 mg
Medium | Elbows Wrists | 10 to 40 mg
Small | Metacarpophalangeal Interphalangeal Sternoclavicular Acromioclavicular | 4 to 10 mg

Procedure: It is recommended that the anatomy of the joint involved be reviewed before attempting intra-articular injection. In order to obtain the full anti-inflammatory effect, it is important that the injection be made into the synovial space. Employing the same sterile technique as for a lumbar puncture, a sterile 20 to 24 gauge needle (on a dry syringe) is quickly inserted into the synovial cavity. Procaine infiltration is elective. The aspiration of only a few drops of joint fluid proves the joint space has been entered by the needle. The injection site for each joint is determined by that location where the synovial cavity is most superficial and most free of large vessels and nerves. With the needle in place, the aspirating syringe is removed and replaced by a second syringe containing the desired amount of DEPO-MEDROL. The plunger is then pulled outward slightly to aspirate synovial fluid and to make sure the needle is still in the synovial space. After injection, the joint is moved gently a few times to aid mixing of the synovial fluid and the suspension. The site is covered with a small sterile dressing.

Suitable sites for intra-articular injection are the knee, ankle, wrist, elbow, shoulder, phalangeal, and hip joints. Since difficulty is not infrequently encountered in entering the hip joint, precautions should be taken to avoid any large blood vessels in the area. Joints not suitable for injection are those that are anatomically inaccessible such as the spinal joints and those like the sacroiliac joints that are devoid of synovial space. Treatment failures are most frequently the result of failure to enter the joint space. Little or no benefit follows injection into surrounding tissue. If failures occur when injections into the synovial spaces are certain, as determined by aspiration of fluid, repeated injections are usually futile.

If a local anesthetic is used prior to injection of DEPO-MEDROL, the anesthetic package insert should be read carefully and all the precautions observed.

2. Bursitis. The area around the injection site is prepared in a sterile way and a wheal at the site made with 1 percent procaine hydrochloride solution. A 20 to 24 gauge needle attached to a dry syringe is inserted into the bursa and the fluid aspirated. The needle is left in place and the aspirating syringe changed for a small syringe containing the desired dose. After injection, the needle is withdrawn and a small dressing applied.

3. Miscellaneous: Ganglion, Tendinitis, Epicondylitis. In the treatment of conditions such as tendinitis or tenosynovitis, care should be taken following application of a suitable antiseptic to the overlying skin to inject the suspension into the tendon sheath rather than into the substance of the tendon. The tendon may be readily palpated when placed on a stretch. When treating conditions such as epicondylitis, the area of greatest tenderness should be outlined carefully and the suspension infiltrated into the area. For ganglia of the tendon sheaths, the suspension is injected directly into the cyst. In many cases, a single injection causes a marked decrease in the size of the cystic tumor and may effect disappearance. The usual sterile precautions should be observed, of course, with each injection.

The dose in the treatment of the various conditions of the tendinous or bursal structures listed above varies with the condition being treated and ranges from 4 to 30 mg. In recurrent or chronic conditions, repeated injections may be necessary.

4. Injections for Local Effect in Dermatologic Conditions. Following cleansing with an appropriate antiseptic such as 70% alcohol, 20 to 60 mg of the suspension is injected into the lesion. It may be necessary to distribute doses ranging from 20 to 40 mg by repeated local injections in the case of large lesions. Care should be taken to avoid injection of sufficient material to cause blanching since this may be followed by a small slough. One to four injections are usually employed, the intervals between injections varying with the type of lesion being treated and the duration of improvement produced by the initial injection.

B. Administration for Systemic Effect

The intramuscular dosage will vary with the condition being treated. When employed as a temporary substitute for oral therapy, a single injection during each 24-hour period of a dose of the suspension equal to the total daily oral dose of MEDROL® Tablets (methylprednisolone tablets, USP) is usually sufficient. When a prolonged effect is desired, the weekly dose may be calculated by multiplying the daily oral dose by 7 and given as a single intramuscular injection.

In pediatric patients, the initial dose of methylprednisolone may vary depending on the specific disease entity being treated. Dosage must be individualized according to the severity of the disease and response of the patient. The recommended dosage may be reduced for pediatric patients, but dosage should be governed by the severity of the condition rather than by strict adherence to the ratio indicated by age or body weight.

In patients with the adrenogenital syndrome, a single intramuscular injection of 40 mg every two weeks may be adequate. For maintenance of patients with rheumatoid arthritis, the weekly intramuscular dose will vary from 40 to 120 mg. The usual dosage for patients with dermatologic lesions benefited by systemic corticoid therapy is 40 to 120 mg of methylprednisolone acetate administered intramuscularly at weekly intervals for one to four weeks. In acute severe dermatitis due to poison ivy, relief may result within 8 to 12 hours following intramuscular administration of a single dose of 80 to 120 mg. In chronic contact dermatitis, repeated injections at 5 to 10 day intervals may be necessary. In seborrheic dermatitis, a weekly dose of 80 mg may be adequate to control the condition.

Following intramuscular administration of 80 to 120 mg to asthmatic patients, relief may result within 6 to 48 hours and persist for several days to two weeks. Similarly, in patients with allergic rhinitis (hay fever), an intramuscular dose of 80 to 120 mg may be followed by relief of coryzal symptoms within six hours persisting for several days to three weeks.

If signs of stress are associated with the condition being treated, the dosage of the suspension should be increased. If a rapid hormonal effect of maximum intensity is required, the intravenous administration of highly soluble methylprednisolone sodium succinate is indicated.

In treatment of acute exacerbations of multiple sclerosis, daily doses of 160 mg of methylprednisolone for a week followed by 64 mg every other day for 1 month have been shown to be effective.

For the purpose of comparison, the following is the equivalent milligram dose of the various glucocorticoids:

Cortisone, 25 | Triamcinolone, 4
Hydrocortisone, 20 | Paramethasone, 2
Prednisolone, 5 | Betamethasone, 0.75
Prednisone, 5 | Dexamethasone, 0.75
Methylprednisolone, 4

These dose relationships apply only to oral or intravenous administration of these compounds. When these substances or their derivatives are injected intramuscularly or into joint spaces, their relative properties may be greatly altered.

HOW SUPPLIED

DEPO-MEDROL Sterile Aqueous Suspension is available as single-dose vials in the following strengths and package sizes:

40 mg per mL |  | 80 mg per mL
1 mL vials | NDC 0009-3073-01 | 1 mL vials | NDC 0009-3475-01
25 × 1 mL vials | NDC 0009-3073-03 | 25 × 1 mL vials | NDC 0009-3475-03

STORAGE AND HANDLING

Store at controlled room temperature 20° to 25°C (68° to 77°F) [see USP].

LAB-0160-7.0
February 2012

AQUEOUS SOLUTIONS FOR INFILTRATION

AND NERVE BLOCK

Ampul

Plastic Multiple-dose Fliptop Vial

Glass Teartop Vial

Rx only

DESCRIPTION

Lidocaine Hydrochloride Injection, USP is a sterile, nonpyrogenic solution of lidocaine hydrochloride in water for injection for parenteral administration in various concentrations with characteristics as follows:

Concentration | 0.5% | 1% | 1.5% | 2%
mg/mL lidocaine HCl (anhyd.) | 5 | 10 | 15 | 20
mg/mL sodium chloride | 8 | 7 | 6.5 | 6

Multiple-dose vials contain 0.1% of methylparaben added as preservative. May contain sodium hydroxide and/or hydrochloric acid for pH adjustment. The pH is 6.5 (5.0 to 7.0). See HOW SUPPLIED section for various sizes and strengths.

Lidocaine is a local anesthetic of the amide type.

Lidocaine Hydrochloride, USP is chemically designated 2-(diethylamino)-N-(2,6-dimethylphenyl)-acetamide monohydrochloride monohydrate, a white powder freely soluble in water. The molecular weight is 288.82. It has the following structural formula:

The semi-rigid vial used for the plastic vials is fabricated from a specially formulated polyolefin. It is a copolymer of ethylene and propylene. The safety of the plastic has been confirmed by tests in animals according to USP biological standards for plastic containers. The container requires no vapor barrier to maintain the proper drug concentration.

CLINICAL PHARMACOLOGY

Mechanism of action: Lidocaine stabilizes the neuronal membrane by inhibiting the ionic fluxes required for the initiation and conduction of impulses, thereby effecting local anesthetic action.

Hemodynamics: Excessive blood levels may cause changes in cardiac output, total peripheral resistance, and mean arterial pressure. With central neural blockade these changes may be attributable to block of autonomic fibers, a direct depressant effect of the local anesthetic agent on various components of the cardiovascular system and/or the beta-adrenergic receptor stimulating action of epinephrine when present. The net effect is normally a modest hypotension when the recommended dosages are not exceeded.

Pharmacokinetics and metabolism: Information derived from diverse formulations, concentrations and usages reveals that lidocaine is completely absorbed following parenteral administration, its rate of absorption depending, for example, upon various factors such as the site of administration and the presence or absence of a vasoconstrictor agent. Except for intravascular administration, the highest blood levels are obtained following intercostal nerve block and the lowest after subcutaneous administration.

The plasma binding of lidocaine is dependent on drug concentration, and the fraction bound decreases with increasing concentration. At concentrations of 1 to 4 mcg of free base per mL, 60 to 80 percent of lidocaine is protein bound. Binding is also dependent on the plasma concentration of the alpha-1-acid glycoprotein.

Lidocaine crosses the blood-brain and placental barriers, presumably by passive diffusion.

Lidocaine is metabolized rapidly by the liver, and metabolites and unchanged drug are excreted by the kidneys. Biotransformation includes oxidative N-dealkylation, ring hydroxylation, cleavage of the amide linkage, and conjugation. N-dealkylation, a major pathway of biotransformation, yields the metabolites monoethylglycinexylidide and glycinexylidide. The pharmacological/toxicological actions of these metabolites are similar to, but less potent than, those of lidocaine. Approximately 90% of lidocaine administered is excreted in the form of various metabolites, and less than 10% is excreted unchanged. The primary metabolite in urine is a conjugate of 4-hydroxy-2, 6-dimethylaniline.

The elimination half-life of lidocaine following an intravenous bolus injection is typically 1.5 to 2.0 hours. Because of the rapid rate at which lidocaine is metabolized, any condition that affects liver function may alter lidocaine kinetics. The half-life may be prolonged two-fold or more in patients with liver dysfunction. Renal dysfunction does not affect lidocaine kinetics but may increase the accumulation of metabolites.

Factors such as acidosis and the use of CNS stimulants and depressants affect the CNS levels of lidocaine required to produce overt systemic effects. Objective adverse manifestations become increasingly apparent with increasing venous plasma levels above 6.0 mcg free base per mL. In the rhesus monkey arterial blood levels of 18-21 mcg/mL have been shown to be threshold for convulsive activity.

INDICATIONS AND USAGE

Lidocaine Hydrochloride Injection, USP is indicated for production of local or regional anesthesia by infiltration techniques such as percutaneous injection and intravenous regional anesthesia by peripheral nerve block techniques such as brachial plexus and intercostal and by central neural techniques such as lumbar and caudal epidural blocks, when the accepted procedures for these techniques as described in standard textbooks are observed.

CONTRAINDICATIONS

Lidocaine is contraindicated in patients with a known history of hypersensitivity to local anesthetics of the amide type.

WARNINGS

LIDOCAINE HYDROCHLORIDE INJECTION, FOR INFILTRATION AND NERVE BLOCK, SHOULD BE EMPLOYED ONLY BY CLINICIANS WHO ARE WELL VERSED IN DIAGNOSIS AND MANAGEMENT OF DOSE-RELATED TOXICITY AND OTHER ACUTE EMERGENCIES THAT MIGHT ARISE FROM THE BLOCK TO BE EMPLOYED AND THEN ONLY AFTER ENSURING THE IMMEDIATE AVAILABILITY OF OXYGEN, OTHER RESUSCITATIVE DRUGS, CARDIOPULMONARY EQUIPMENT, AND THE PERSONNEL NEEDED FOR PROPER MANAGEMENT OF TOXIC REACTIONS AND RELATED EMERGENCIES (See also ADVERSE REACTIONS and PRECAUTIONS). DELAY IN PROPER MANAGEMENT OF DOSE-RELATED TOXICITY, UNDERVENTILATION FROM ANY CAUSE AND/OR ALTERED SENSITIVITY MAY LEAD TO THE DEVELOPMENT OF ACIDOSIS, CARDIAC ARREST AND, POSSIBLY, DEATH.

Intra-articular infusions of local anesthetics following arthroscopic and other surgical procedures is an unapproved use, and there have been post-marketing reports of chondrolysis in patients receiving such infusions. The majority of reported cases of chondrolysis have involved the shoulder joint; cases of gleno-humeral chondrolysis have been described in pediatric and adult patients following intra-articular infusions of local anesthetics with and without epinephrine for periods of 48 to 72 hours. There is insufficient information to determine whether shorter infusion periods are not associated with these findings. The time of onset of symptoms, such as joint pain, stiffness and loss of motion can be variable, but may begin as early as the 2nd month after surgery. Currently, there is no effective treatment for chondrolysis; patients who experienced chondrolysis have required additional diagnostic and therapeutic procedures and some required arthroplasty or shoulder replacement.

To avoid intravascular injection, aspiration should be performed before the local anesthetic solution is injected. The needle must be repositioned until no return of blood can be elicited by aspiration. Note, however, that the absence of blood in the syringe does not guarantee that intravascular injection has been avoided.

Local anesthetic solutions containing antimicrobial preservatives (e.g., methylparaben) should not be used for epidural or spinal anesthesia because the safety of these agents has not been established with regard to intrathecal injection, either intentional or accidental.

PRECAUTIONS

General:

The safety and effectiveness of lidocaine depend on proper dosage, correct technique, adequate precautions, and readiness for emergencies. Standard textbooks should be consulted for specific techniques and precautions for various regional anesthetic procedures.

Resuscitative equipment, oxygen, and other resuscitative drugs should be available for immediate use. (See WARNINGS and ADVERSE REACTIONS). The lowest dosage that results in effective anesthesia should be used to avoid high plasma levels and serious adverse effects. Syringe aspirations should also be performed before and during each supplemental injection when using indwelling catheter techniques. During the administration of epidural anesthesia, it is recommended that a test dose be administered initially and that the patient be monitored for central nervous system toxicity and cardiovascular toxicity, as well as for signs of unintended intrathecal administration before proceeding. When clinical conditions permit, consideration should be given to employing local anesthetic solutions that contain epinephrine for the test dose because circulatory changes compatible with epinephrine may also serve as a warning sign of unintended intravascular injection. An intravascular injection is still possible even if aspirations for blood are negative. Repeated doses of lidocaine may cause significant increases in blood levels with each repeated dose because of slow accumulation of the drug or its metabolites. Tolerance to elevated blood levels varies with the status of the patient. Debilitated, elderly patients, acutely ill patients and children should be given reduced doses commensurate with their age and physical condition. Lidocaine should also be used with caution in patients with severe shock or heart block. Lumbar and caudal epidural anesthesia should be used with extreme caution in persons with the following conditions: existing neurological disease, spinal deformities, septicemia and severe hypertension.

Local anesthetic solutions containing a vasoconstrictor should be used cautiously and in carefully circumscribed quantities in areas of the body supplied by end arteries or having otherwise compromised blood supply. Patients with peripheral vascular disease and those with hypertensive vascular disease may exhibit exaggerated vasoconstrictor response. Ischemic injury or necrosis may result. Preparations containing a vasoconstrictor should be used with caution in patients during or following the administration of potent general anesthetic agents, since cardiac arrhythmias may occur under such conditions.

Careful and constant monitoring of cardiovascular and respiratory (adequacy of ventilation) vital signs and the patient’s state of consciousness should be accomplished after each local anesthetic injection. It should be kept in mind at such times that restlessness, anxiety, tinnitus, dizziness, blurred vision, tremors, depression or drowsiness may be early warning signs of central nervous system toxicity.

Since amide-type local anesthetics are metabolized by the liver, lidocaine should be used with caution in patients with hepatic disease. Patients with severe hepatic disease, because of their inability to metabolize local anesthetics normally, are at greater risk of developing toxic plasma concentrations. Lidocaine should also be used with caution in patients with impaired cardiovascular function since they may be less able to compensate for functional changes associated with the prolongation of A-V conduction produced by these drugs. Many drugs used during the conduct of anesthesia are considered potential triggering agents for familial malignant hyperthermia. Since it is not known whether amide-type local anesthetics may trigger this reaction and since the need for supplemental general anesthesia cannot be predicted in advance, it is suggested that a standard protocol for the management of malignant hyperthermia should be available. Early unexplained signs of tachycardia, tachypnea, labile blood pressure and metabolic acidosis may precede temperature elevation. Successful outcome is dependent on early diagnosis, prompt discontinuance of the suspect triggering agent(s) and institution of treatment, including oxygen therapy, indicated supportive measures and dantrolene (consult dantrolene sodium intravenous package insert before using).

Proper tourniquet technique, as described in publications and standard textbooks, is essential in the performance of intravenous regional anesthesia. Solutions containing epinephrine or other vasoconstrictors should not be used for this technique.

Lidocaine should be used with caution in persons with known drug sensitivities. Patients allergic to para-aminobenzoic acid derivatives (procaine, tetracaine, benzocaine, etc.) have not shown cross sensitivity to lidocaine.

Use in the Head and Neck Area: Small doses of local anesthetics injected into the head and neck area, including retrobulbar, dental and stellate ganglion blocks, may produce adverse reactions similar to systemic toxicity seen with unintentional intravascular injections of larger doses. Confusion, convulsions, respiratory depression and/or respiratory arrest and cardiovascular stimulation or depression have been reported. These reactions may be due to intra-arterial injections of the local anesthetic with retrograde flow to the cerebral circulation. Patients receiving these blocks should have their circulation and respiration monitored and be constantly observed. Resuscitative equipment and personnel for treating adverse reactions should be immediately available. Dosage recommendations should not be exceeded. (See DOSAGE AND ADMINISTRATION).

Information for Patients:

When appropriate, patients should be informed in advance that they may experience temporary loss of sensation and motor activity, usually in the lower half of the body following proper administration of epidural anesthesia.

Clinically Significant Drug Interactions:

The administration of local anesthetic solutions containing epinephrine or norepinephrine to patients receiving monoamine oxidase inhibitors or tricyclic antidepressants may produce severe prolonged hypertension.

Phenothiazines and butyrophenones may reduce or reverse the pressor effect of epinephrine.

Concurrent use of these agents should generally be avoided. In situations when concurrent therapy is necessary, careful patient monitoring is essential.

Concurrent administration of vasopressor drugs (for the treatment of hypotension related to obstetric blocks) and ergot-type oxytoxic drugs may cause severe persistent hypertension or cerebrovascular accidents.

Drug Laboratory Test Interactions:

The intramuscular injection of lidocaine may result in an increase in creatine phosphokinase levels. Thus, the use of this enzyme determination without isoenzyme separation as a diagnostic test for the presence of acute myocardial infarction may be compromised by the intramuscular injection of lidocaine.

Carcinogenesis, Mutagenesis, Impairment of Fertility:

Studies of lidocaine in animals to evaluate the carcinogenic and mutagenic potential or the effect on fertility have not been conducted.

Pregnancy:

Teratogenic Effects. Pregnancy Category B. Reproduction studies have been performed in rats at doses up to 6.6 times the human dose and have revealed no evidence of harm to the fetus caused by lidocaine. There are, however, no adequate and well-controlled studies in pregnant women. Animal reproduction studies are not always predictive of human response. General consideration should be given to this fact before administering lidocaine to women of childbearing potential, especially during early pregnancy when maximum organogenesis takes place.

Labor and Delivery:

Local anesthetics rapidly cross the placenta and when used for epidural, paracervical, pudendal or caudal block anesthesia, can cause varying degrees of maternal, fetal and neonatal toxicity (See CLINICAL PHARMACOLOGY—Pharmacokinetics). The potential for toxicity depends upon the procedure performed, the type and amount of drug used, and the technique of drug administration. Adverse reactions in the parturient, fetus and neonate involve alterations of the central nervous system peripheral vascular tone and cardiac function.

Maternal hypotension has resulted from regional anesthesia. Local anesthetics produce vasodilation by blocking sympathetic nerves. Elevating the patient’s legs and positioning her on her left side will help prevent decreases in blood pressure. The fetal heart rate also should be monitored continuously, and electronic fetal monitoring is highly advisable.

Epidural, spinal, paracervical, or pudendal anesthesia may alter the forces of parturition through changes in uterine contractility or maternal expulsive efforts. In one study, paracervical block anesthesia was associated with a decrease in the mean duration of first stage labor and facilitation of cervical dilation. However, spinal and epidural anesthesia have also been reported to prolong the second stage of labor by removing the parturient’s reflex urge to bear down or by interfering with motor function. The use of obstetrical anesthesia may increase the need for forceps assistance.

The use of some local anesthetic drug products during labor and delivery may be followed by diminished muscle strength and tone for the first day or two of life. The long-term significance of these observations is unknown. Fetal bradycardia may occur in 20 to 30 percent of patients receiving paracervical nerve block anesthesia with the amide-type local anesthetics and may be associated with fetal acidosis. Fetal heart rate should always be monitored during paracervical anesthesia. The physician should weigh the possible advantages against risks when considering paracervical block in prematurity, toxemia of pregnancy and fetal distress. Careful adherence to recommended dosage is of the utmost importance in obstetrical paracervical block. Failure to achieve adequate analgesia with recommended doses should arouse suspicion of intravascular or fetal intracranial injection. Cases compatible with unintended fetal intracranial injection of local anesthetic solution have been reported following intended paracervical or pudendal block or both. Babies so affected present with unexplained neonatal depression at birth, which correlates with high local anesthetic serum levels, and often manifest seizures within six hours. Prompt use of supportive measures combined with forced urinary excretion of the local anesthetic has been used successfully to manage this complication.

Case reports of maternal convulsions and cardiovascular collapse following use of some local anesthetics for paracervical block in early pregnancy (as anesthesia for elective abortion) suggest that systemic absorption under these circumstances may be rapid. The recommended maximum dose of each drug should not be exceeded. Injection should be made slowly and with frequent aspiration. Allow a 5-minute interval between sides.

Nursing Mothers:

It is not known whether this drug is excreted in human milk. Because many drugs are excreted in human milk, caution should be exercised when lidocaine is administered to a nursing woman.

Pediatric Use:

Dosages in pediatric patients should be reduced, commensurate with age, body weight and physical condition. See DOSAGE AND ADMINISTRATION.

ADVERSE REACTIONS

Systemic: Adverse experiences following the administration of lidocaine are similar in nature to those observed with other amide local anesthetic agents. These adverse experiences are, in general, dose-related and may result from high plasma levels caused by excessive dosage, rapid absorption or inadvertent intravascular injection, or may result from a hypersensitivity, idiosyncrasy or diminished tolerance on the part of the patient. Serious adverse experiences are generally systemic in nature. The following types are those most commonly reported:

Central Nervous System: CNS manifestations are excitatory and/or depressant and may be characterized by lightheadedness, nervousness, apprehension, euphoria, confusion, dizziness, drowsiness, tinnitus, blurred or double vision, vomiting, sensations of heat, cold or numbness, twitching, tremors, convulsions, unconsciousness, respiratory depression and arrest. The excitatory manifestations may be very brief or may not occur at all, in which case the first manifestation of toxicity may be drowsiness merging into unconsciousness and respiratory arrest.

Drowsiness following the administration of lidocaine is usually an early sign of a high blood level of the drug and may occur as a consequence of rapid absorption.

Cardiovascular System: Cardiovascular manifestations are usually depressant and are characterized by bradycardia, hypotension, and cardiovascular collapse, which may lead to cardiac arrest.

Allergic: Allergic reactions are characterized by cutaneous lesions, urticaria, edema or anaphylactoid reactions. Allergic reactions may occur as a result of sensitivity either to local anesthetic agents or to the methylparaben used as a preservative in multiple dose vials. Allergic reactions as a result of sensitivity to lidocaine are extremely rare and, if they occur, should be managed by conventional means. The detection of sensitivity by skin testing is of doubtful value.

Neurologic: The incidences of adverse reactions associated with the use of local anesthetics may be related to the total dose of local anesthetic administered and are also dependent upon the particular drug used, the route of administration and the physical status of the patient. In a prospective review of 10,440 patients who received lidocaine for spinal anesthesia, the incidences of adverse reactions were reported to be about 3 percent each for positional headaches, hypotension and backache; 2 percent for shivering; and less than 1 percent each for peripheral nerve symptoms, nausea, respiratory inadequacy and double vision. Many of these observations may be related to local anesthetic techniques, with or without a contribution from the local anesthetic.

In the practice of caudal or lumbar epidural block, occasional unintentional penetration of the subarachnoid space by the catheter may occur. Subsequent adverse effects may depend partially on the amount of drug administered subdurally.

These may include spinal block of varying magnitude (including total spinal block), hypotension secondary to spinal block, loss of bladder and bowel control, and loss of perineal sensation and sexual function. Persistent motor, sensory and/or autonomic (sphincter control) deficit of some lower spinal segments with slow recovery (several months) or incomplete recovery have been reported in rare instances when caudal or lumbar epidural block has been attempted. Backache and headache have also been noted following use of these anesthetic procedures.

There have been reported cases of permanent injury to extraocular muscles requiring surgical repair following retrobulbar administration.

OVERDOSAGE

Acute emergencies from local anesthetics are generally related to high plasma levels encountered during therapeutic use of local anesthetics or to unintended subarachnoid injection of local anesthetic solution (see ADVERSE REACTIONS, WARNINGS and PRECAUTIONS).

Management of Local Anesthetic Emergencies: The first consideration is prevention, best accomplished by careful monitoring of cardiovascular and respiratory vital signs and the patient’s state of consciousness after each local anesthetic injection. At the first sign of change, oxygen should be administered.

The first step in the management of convulsions, as well as underventilation or apnea due to unintended subarachnoid injection of drug solution, consists of immediate attention to the maintenance of a patent airway and assisted or controlled ventilation with oxygen and a delivery system capable of permitting immediate positive airway pressure by mask. Immediately after the institution of these ventilatory measures, the adequacy of the circulation should be evaluated, keeping in mind that drugs used to treat convulsions sometimes depress the circulation when administered intravenously. Should convulsions persist despite adequate respiratory support, and if the status of the circulation permits, small increments of an ultra-short acting barbiturate (such as thiopental or thiamylal) or a benzodiazepine (such as diazepam) may be administered intravenously. The clinician should be familiar, prior to use of local anesthetics, with these anticonvulsant drugs. Supportive treatment of circulatory depression may require administration of intravenous fluids and, when appropriate, a vasopressor as directed by the clinical situation (e.g., ephedrine).

If not treated immediately, both convulsions and cardiovascular depression can result in hypoxia, acidosis, bradycardia, arrhythmias and cardiac arrest. Underventilation or apnea due to unintentional subarachnoid injection of local anesthetic solution may produce these same signs and also lead to cardiac arrest if ventilatory support is not instituted. If cardiac arrest should occur standard cardiopulmonary resuscitative measures should be instituted.

Endotracheal intubation, employing drugs and techniques familiar to the clinician, may be indicated, after initial administration of oxygen by mask, if difficulty is encountered in the maintenance of a patent airway or if prolonged ventilatory support (assisted or controlled) is indicated.

Dialysis is of negligible value in the treatment of acute overdosage with lidocaine.

The oral LD50 of lidocaine HCl in non-fasted female rats is 459 (346−773) mg/kg (as the salt) and 214 (159−324) mg/kg (as the salt) in fasted female rats.

DOSAGE AND ADMINISTRATION

Table 1 (Recommended Dosages) summarizes the recommended volumes and concentrations of Lidocaine Hydrochloride Injection, USP for various types of anesthetic procedures. The dosages suggested in this table are for normal healthy adults and refer to the use of epinephrine-free solutions. When larger volumes are required only solutions containing epinephrine should be used, except in those cases where vasopressor drugs may be contraindicated.

There have been adverse event reports of chondrolysis in patients receiving intra-articular infusions of local anesthetics following arthroscopic and other surgical procedures. Lidocaine is not approved for this use (see WARNINGS and DOSAGE AND ADMINISTRATION).

These recommended doses serve only as a guide to the amount of anesthetic required for most routine procedures. The actual volumes and concentrations to be used depend on a number of factors such as type and extent of surgical procedure, depth of anesthesia and degree of muscular relaxation required, duration of anesthesia required, and the physical condition of the patient. In all cases the lowest concentration and smallest dose that will produce the desired result should be given. Dosages should be reduced for children and for elderly and debilitated patients and patients with cardiac and/or liver disease.

The onset of anesthesia, the duration of anesthesia and the degree of muscular relaxation are proportional to the volume and concentration (i.e., total dose) of local anesthetic used. Thus, an increase in volume and concentration of Lidocaine Hydrochloride Injection will decrease the onset of anesthesia, prolong the duration of anesthesia, provide a greater degree of muscular relaxation and increase the segmental spread of anesthesia. However, increasing the volume and concentration of Lidocaine Hydrochloride Injection may result in a more profound fall in blood pressure when used in epidural anesthesia. Although the incidence of side effects with lidocaine is quite low, caution should be exercised when employing large volumes and concentrations, since the incidence of side effects is directly proportional to the total dose of local anesthetic agent injected.

For intravenous regional anesthesia, only the 50 mL single-dose vial containing 0.5% Lidocaine Hydrochloride Injection, USP should be used.

Epidural Anesthesia

For epidural anesthesia, only the following available specific products of Lidocaine Hydrochloride Injection by Hospira are recommended:

1%. . . . . . . . . . . . . . . . . . . . 30 mL single-dose teartop vials

1.5%. . . . . . . . . . . . . . . . . . . . . . . 20 mL single-dose ampuls

2%. . . . . . . . . . . . . . . . . . . . . . . . . 10 mL single-dose ampuls

Although these solutions are intended specifically for epidural anesthesia, they may also be used for infiltration and peripheral nerve block provided they are employed as single dose units. These solutions contain no bacteriostatic agent. In epidural anesthesia, the dosage varies with the number of dermatomes to be anesthetized (generally 2−3 mL of the indicated concentration per dermatome).

Caudal and Lumbar Epidural Block: As a precaution against the adverse experiences sometimes observed following unintentional penetration of the subarachnoid space, a test dose such as 2−3 mL of 1.5% lidocaine hydrochloride should be administered at least 5 minutes prior to injecting the total volume required for a lumbar or caudal epidural block. The test dose should be repeated if the patient is moved in a manner that may have displaced the catheter. Epinephrine, if contained in the test dose (10−15 mcg have been suggested), may serve as a warning of unintentional intravascular injection. If injected into a blood vessel, this amount of epinephrine is likely to produce a transient "epinephrine response" within 45 seconds, consisting of an increase in heart rate and systolic blood pressure, circumoral pallor, palpitations and nervousness in the unsedated patient. The sedated patient may exhibit only a pulse rate increase of 20 or more beats per minute for 15 or more seconds. Patients on beta-blockers may not manifest changes in heart rate, but blood pressure monitoring can detect an evanescent rise in systolic blood pressure. Adequate time should be allowed for onset of anesthesia after administration of each test dose. The rapid injection of a large volume of Lidocaine Hydrochloride Injection through the catheter should be avoided, and, when feasible, fractional doses should be administered.

In the event of the known injection of a large volume of local anesthetic solutions into the subarachnoid space, after suitable resuscitation and if the catheter is in place, consider attempting the recovery of drug by draining a moderate amount of cerebrospinal fluid (such as 10 mL) through the epidural catheter.

Maximum Recommended Dosages

NOTE: The products accompanying this insert do not contain epinephrine.

Adults: For normal healthy adults, the individual maximum recommended dose of lidocaine HCl with epinephrine should not exceed 7 mg/kg (3.5 mg/lb) of body weight and in general it is recommended that the maximum total dose not exceed 500 mg. When used without epinephrine, the maximum individual dose should not exceed 4.5 mg/kg (2 mg/lb) of body weight and in general it is recommended that the maximum total dose does not exceed 300 mg. For continuous epidural or caudal anesthesia, the maximum recommended dosage should not be administered at intervals of less than 90 minutes. When continuous lumbar or caudal epidural anesthesia is used for non-obstetrical procedures, more drug may be administered if required to produce adequate anesthesia.

The maximum recommended dose per 90 minute period of lidocaine hydrochloride for paracervical block in obstetrical patients and non-obstetrical patients is 200 mg total. One-half of the total dose is usually administered to each side. Inject slowly five minutes between sides. (See also discussion of paracervical block in PRECAUTIONS).

For intravenous regional anesthesia, the dose administered should not exceed 4 mg/kg in adults.

Children: It is difficult to recommend a maximum dose of any drug for children, since this varies as a function of age and weight. For children over 3 years of age who have a normal lean body mass and normal body development, the maximum dose is determined by the child’s age and weight. For example, in a child of 5 years weighing 50 lbs., the dose of lidocaine HCl should not exceed 75 — 100 mg (1.5 — 2 mg/lb). The use of even more dilute solutions (i.e., 0.25 — 0.5%) and total dosages not to exceed 3 mg/kg (1.4 mg/lb) are recommended for induction of intravenous regional anesthesia in children.

In order to guard against systemic toxicity, the lowest effective concentration and lowest effective dose should be used at all times. In some cases it will be necessary to dilute available concentrations with 0.9% sodium chloride injection in order to obtain the required final concentration.

Parenteral drug products should be inspected visually for particulate matter and discoloration prior to administration whenever the solution and container permit. Solutions that are discolored and/or contain particulate matter should not be used.

Table 1
Recommended Dosages of Lidocaine Hydrochloride Injection, USP for Various Anesthetic
Procedures in Normal Healthy Adults
 | Lidocaine Hydrochloride Injection, USP (without Epinephrine)
Procedure | Conc. (%) | Vol. (mL) | Total Dose (mg)
Infiltration
Percutaneous | 0.5 or 1.0 | 1−60 | 5−300
Intravenous Regional | 0.5 | 10−60 | 50−300
Peripheral Nerve Blocks, e.g.
Brachial | 1.5 | 15−20 | 225−300
Dental | 2.0 | 1−5 | 20−100
Intercostal | 1.0 | 3 | 30
Paravertebral | 1.0 | 3−5 | 30−50
Pudendal (each side) | 1.0 | 10 | 100
Paracervical
Obstetrical Analgesia
(each side) | 1.0 | 10 | 100
Sympathetic Nerve Blocks, e.g.
Cervical (stellate ganglion) | 1.0 | 5 | 50
Lumbar | 1.0 | 5−10 | 50−100
Central Neural Blocks
Epidural*
Thoracic | 1.0 | 20−30 | 200−300
Lumbar
Analgesia | 1.0 | 25−30 | 250−300
Anesthesia | 1.5 | 15−20 | 225−300
 | 2.0 | 10−15 | 200−300
Caudal
Obstetrical Analgesia | 1.0 | 20−30 | 200−300
Surgical Anesthesia | 1.5 | 15−20 | 225−300
*Dose determined by number of dermatomes to be anesthetized (2 to 3 mL/dermatome).

THE ABOVE SUGGESTED CONCENTRATIONS AND VOLUMES SERVE ONLY AS A GUIDE. OTHER VOLUMES AND CONCENTRATIONS MAY BE USED PROVIDED THE TOTAL MAXIMUM RECOMMENDED DOSE IS NOT EXCEEDED.

Sterilization, Storage and Technical Procedures: Disinfecting agents containing heavy metals, which cause release of respective ions (mercury, zinc, copper, etc.) should not be used for skin or mucous membrane disinfection as they have been related to incidence of swelling and edema. When chemical disinfection of multi-dose vials is desired, either isopropyl alcohol (91%) or 70% ethyl alcohol is recommended. Many commercially available brands of rubbing alcohol, as well as solutions of ethyl alcohol not of USP grade, contain denaturants which are injurious to rubber and, therefore, are not to be used. It is recommended that chemical disinfection be accomplished by wiping the vial stopper thoroughly with cotton or gauze that has been moistened with the recommended alcohol just prior to use.

HOW SUPPLIED

Lidocaine Hydrochloride Injection, USP is supplied as follows:

NDC | Container | Concentration | Size | Total (mg)
Single-dose:
0409-4278-01 | Glass Teartop Vial | 0.5% (5 mg/mL) | 50 mL | 250
0409-4713-01 | Glass Ampul | 1% (10 mg/mL) | 2 mL (bulk – 400 units) | 20
0409-4713-02 | Glass Ampul | 1% (10 mg/mL) | 5 mL | 50
0409-4713-05 | Glass Ampul | 1% (10 mg/mL) | 5 mL (bulk – 400 units) | 50
0409-4713-20 | Glass Ampul | 1% (10 mg/mL) | 20 mL | 200
0409-4713-32 | Glass Ampul | 1% (10 mg/mL) | 2 mL | 20
0409-4713-62 | Glass Ampul | 1% (10 mg/mL) | 2 mL (bulk – 800 units) | 20
0409-4713-65 | Glass Ampul | 1% (10 mg/mL) | 5 mL (bulk – 800 units) | 50
0409-4279-02 | Glass Teartop Vial | 1% (10 mg/mL) | 30 mL | 300
0409-4270-01 | Sterile Glass Teartop Vial | 1% (10 mg/mL) | 30 mL | 300
0409-4776-01 | Glass Ampul | 1.5% (15 mg/mL) | 20 mL | 300
0409-4056-01 | Sterile Glass Ampul | 1.5% (15 mg/mL) | 20 mL | 300
0409-4282-01 | Glass Ampul | 2% (20 mg/mL) | 2 mL | 40
0409-4282-02 | Glass Ampul | 2% (20 mg/mL) | 10 mL | 200
Multiple-dose:
0409-4275-01 | Plastic Fliptop Vial | 0.5% (5 mg/mL) | 50 mL | 250
0409-4276-01 | Plastic Fliptop Vial | 1% (10 mg/mL) | 20 mL | 200
0409-4276-02 | Plastic Fliptop Vial | 1% (10 mg/mL) | 50 mL | 500
0409-4277-01 | Plastic Fliptop Vial | 2% (20 mg/mL) | 20 mL | 400
0409-4277-02 | Plastic Fliptop Vial | 2% (20 mg/mL) | 50 mL | 1000

Single-dose products are preservative-free.

Store at 20 to 25°C (68 to 77°F). [See USP Controlled Room Temperature.]

Lidocaine Hydrochloride Injection, USP solutions packaged in ampuls and glass teartop vials may be autoclaved one time only. Autoclave at 15 pounds pressure, 121°C (250°F) for 15 minutes. DO NOT AUTOCLAVE PRODUCT IN PLASTIC VIALS.

Revised: February, 2010

Printed in USA EN-2421

Hospira, Inc., Lake Forest, IL 60045 USA

Principal Display Panel – Vial Label

NDC 0009-3073-01

1 mL Single-Dose Vial

Depo-Medrol®

(methylprednisolone

acetate injectable

suspension, USP)

40 mg/mL

Rx only

Principal Display Panel – Ampule Label

2mL NDC 0409-4713-32

Preservative-Free Rx only

1% LIDOCAINE HCl

Injection, USP

10 mg/mL

RL-1045 (11/04)

HOSPIRA, INC., LK. FOREST, IL 60045 USA

Principal Display Panel –

NDC:53329-820-09

CURAD®

WE HELP HEAL

ALCOHOL SWABS

With 70% isopropyl alcohol

Sterility guaranteed

(unless package is damaged or opened)

Antiseptic

For external use only.

Principal Display Panel – Kit Label

NDC 63187-350-01 RX-Only

Multi-Specialty Kit

Kit Contains:
1 Depo-Medrol® 40mg/mL (1mL)
2 Lidocaine HCl Injection, USP 1% (2mL)
6 Isopropyl Alcohol 70% Prep Pads
1 Pair Nitrile Powder Free Sterile Gloves (Size 7.5)
1 Adhesive Bandage
Non Sterile 4x4 Gauze

Relabeled by:
Proficient Rx LP
Thousand Oaks, CA 91320

LOT:

EXP: